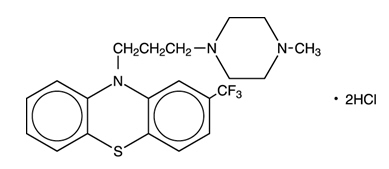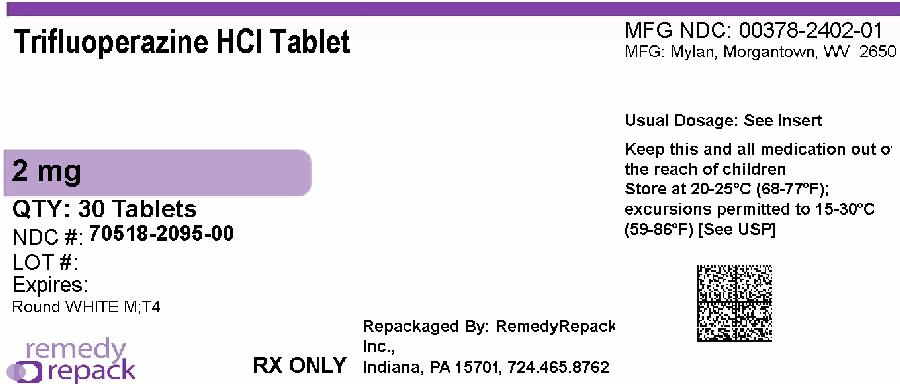 DRUG LABEL: Trifluoperazine Hydrochloride
NDC: 70518-2095 | Form: TABLET, FILM COATED
Manufacturer: REMEDYREPACK INC.
Category: prescription | Type: HUMAN PRESCRIPTION DRUG LABEL
Date: 20260130

ACTIVE INGREDIENTS: TRIFLUOPERAZINE HYDROCHLORIDE 2 mg/1 1
INACTIVE INGREDIENTS: SILICON DIOXIDE; CROSCARMELLOSE SODIUM; HYPROMELLOSE, UNSPECIFIED; LACTOSE MONOHYDRATE; MAGNESIUM STEARATE; MICROCRYSTALLINE CELLULOSE; POLYDEXTROSE; POLYETHYLENE GLYCOL, UNSPECIFIED; STARCH, CORN; SODIUM LAURYL SULFATE; TITANIUM DIOXIDE; TRIACETIN

WARNING

Increased Mortality in Elderly Patients with Dementia-Related Psychosis

Elderly patients with dementia-related psychosis treated with antipsychotic drugs are at an increased risk of death. Analyses of seventeen placebo-controlled trials (modal duration of 10 weeks), largely in patients taking atypical antipsychotic drugs, revealed a risk of death in drug-treated patients of between 1.6 to 1.7 times the risk of death in placebo-treated patients. Over the course of a typical 10-week controlled trial, the rate of death in drug-treated patients was about 4.5%, compared to a rate of about 2.6% in the placebo group. Although the causes of death were varied, most of the deaths appeared to be either cardiovascular (e.g., heart failure, sudden death) or infectious (e.g., pneumonia) in nature. Observational studies suggest that, similar to atypical antipsychotic drugs, treatment with conventional antipsychotic drugs may increase mortality. The extent to which the findings of increased mortality in observational studies may be attributed to the antipsychotic drug as opposed to some characteristic(s) of the patients is not clear. Trifluoperazine hydrochloride is not approved for the treatment of patients with dementia-related psychosis (see WARNINGS).

DESCRIPTION

Each film-coated tablet, for oral administration, contains trifluoperazine hydrochloride, USP equivalent to 1 mg, 2 mg, 5 mg, or 10 mg trifluoperazine.

The structural formula is:

10-[3-(4-Methyl-1-piperazinyl)propyl]-2-(trifluoromethyl) phenothiazine dihydrochloride

In addition, each tablet contains the following inactive ingredients: colloidal silicon dioxide, croscarmellose sodium, hypromellose, lactose monohydrate, magnesium stearate, microcrystalline cellulose, polydextrose, polyethylene glycol, pregelatinized starch (corn), sodium lauryl sulfate, titanium dioxide, and triacetin. The 5 mg and 10 mg tablets also contain D&C Red No. 30 Aluminum Lake, FD&C Blue No. 2 Aluminum Lake and FD&C Yellow No. 6 Aluminum Lake.

INDICATIONS AND USAGE

For the management of schizophrenia.

Trifluoperazine hydrochloride tablets, USP are effective for the short-term treatment of generalized non-psychotic anxiety. However, trifluoperazine hydrochloride tablets are not the first drug to be used in therapy for most patients with non-psychotic anxiety because certain risks associated with its use are not shared by common alternative treatments (i.e., benzodiazepines).

When used in the treatment of non-psychotic anxiety, trifluoperazine hydrochloride tablets should not be administered at doses of more than 6 mg per day or for longer than 12 weeks because the use of trifluoperazine hydrochloride tablets at higher doses or for longer intervals may cause persistent tardive dyskinesia that may prove irreversible (see WARNINGS).

The effectiveness of trifluoperazine hydrochloride tablets as a treatment for non-psychotic anxiety was established in a 4-week clinical multicenter study of outpatients with generalized anxiety disorder (DSM-III). This evidence does not predict that trifluoperazine hydrochloride tablets will be useful in patients with other non-psychotic conditions in which anxiety, or signs that mimic anxiety, are found (i.e., physical illness, organic mental conditions, agitated depression, character pathologies, etc.).

Trifluoperazine hydrochloride tablets have not been shown effective in the management of behavioral complications in patients with mental retardation.

CONTRAINDICATIONS

A known hypersensitivity to phenothiazines, comatose or greatly depressed states due to central nervous system depressants and, in cases of existing blood dyscrasias, bone marrow depression and preexisting liver damage.

WARNINGS

Increased Mortality in Elderly Patients with Dementia-Related Psychosis

Elderly patients with dementia-related psychosis treated with antipsychotic drugs are at an increased risk of death. Trifluoperazine hydrochloride is not approved for the treatment of patients with dementia-related psychosis (see BOXED WARNING).

Tardive Dyskinesia

Tardive dyskinesia, a syndrome consisting of potentially irreversible, involuntary, dyskinetic movements, may develop in patients treated with antipsychotic drugs. Although the prevalence of the syndrome appears to be highest among the elderly, especially elderly women, it is impossible to rely upon prevalence estimates to predict, at the inception of antipsychotic treatment, which patients are likely to develop the syndrome. Whether antipsychotic drug products differ in their potential to cause tardive dyskinesia is unknown.

Both the risk of developing the syndrome and the likelihood that it will become irreversible are believed to increase as the duration of treatment and the total cumulative dose of antipsychotic drugs administered to the patient increase. However, the syndrome can develop, although much less commonly, after relatively brief treatment periods at low doses.

There is no known treatment for established cases of tardive dyskinesia, although the syndrome may remit, partially or completely, if antipsychotic treatment is withdrawn. Antipsychotic treatment itself, however, may suppress (or partially suppress) the signs and symptoms of the syndrome and thereby may possibly mask the underlying disease process. The effect that symptomatic suppression has upon the long-term course of the syndrome is unknown.

Given these considerations, antipsychotics should be prescribed in a manner that is most likely to minimize the occurrence of tardive dyskinesia. Chronic antipsychotic treatment should generally be reserved for patients who suffer from a chronic illness that 1) is known to respond to antipsychotic drugs, and, 2) for whom alternative, equally effective, but potentially less harmful treatments are notavailable or appropriate. In patients who do require chronic treatment, the smallest dose and the shortest duration of treatment producing a satisfactory clinical response should be sought. The need for continued treatment should be reassessed periodically.

If signs and symptoms of tardive dyskinesia appear in a patient on antipsychotics, drug discontinuation should be considered. However, some patients may require treatment despite the presence of the syndrome.

For further information about the description of tardive dyskinesia and its clinical detection, please refer to the sections on PRECAUTIONSand ADVERSE REACTIONS.

Neuroleptic Malignant Syndrome (NMS)

A potentially fatal symptom complex sometimes referred to as Neuroleptic Malignant Syndrome (NMS) has been reported in association with antipsychotic drugs. Clinical manifestations of NMS are hyperpyrexia, muscle rigidity, altered mental status and evidence of autonomic instability (irregular pulse or blood pressure, tachycardia, diaphoresis, and cardiac dysrhythmias).

The diagnostic evaluation of patients with this syndrome is complicated. In arriving at a diagnosis, it is important to identify cases where the clinical presentation includes both serious medical illness (e.g., pneumonia, systemic infection, etc.) and untreated or inadequately treated extrapyramidal signs and symptoms (EPS). Other important considerations in the differential diagnosis include central anticholinergic toxicity, heat stroke, drug fever and primary central nervous system (CNS) pathology.

The management of NMS should include 1) immediate discontinuation of antipsychotic drugs and other drugs not essential to concurrent therapy, 2) intensive symptomatic treatment and medical monitoring, and 3) treatment of any concomitant serious medical problems for which specific treatments are available. There is no general agreement about specific pharmacological treatment regimens for uncomplicated NMS.

If a patient requires antipsychotic drug treatment after recovery from NMS, the potential reintroduction of drug therapy should be carefully considered. The patient should be carefully monitored, since recurrences of NMS have been reported.

An encephalopathic syndrome (characterized by weakness, lethargy, fever, tremulousness and confusion, extrapyramidal symptoms, leukocytosis, elevated serum enzymes, BUN and FBS) has occurred in a few patients treated with lithium plus an antipsychotic. In some instances, the syndrome was followed by irreversible brain damage. Because of a possible causal relationship between these events and the concomitant administration of lithium and antipsychotics, patients receiving such combined therapy should be monitored closely for early evidence of neurologic toxicity and treatment discontinued promptly if such signs appear. This encephalopathic syndrome may be similar to or the same as neuroleptic malignant syndrome (NMS).

Patients who have demonstrated a hypersensitivity reaction (e.g., blood dyscrasias, jaundice) with a phenothiazine should not be reexposed to any phenothiazine, including trifluoperazine hydrochloride, unless in the judgment of the physician the potential benefits of treatment outweigh the possible hazard.

Trifluoperazine hydrochloride may impair mental and/or physical abilities, especially during the first few days of therapy. Therefore, caution patients about activities requiring alertness (e.g., operating vehicles or machinery).

If agents such as sedatives, narcotics, anesthetics, tranquilizers or alcohol are used either simultaneously or successively with the drug, the possibility of an undesirable additive depressant effect should be considered.

Falls

Trifluoperazine hydrochloride tablets may cause somnolence, postural hypotension, motor and sensory instability, which may lead to falls and, consequently, fractures or other injuries. For patients with diseases, conditions, or medications that could exacerbate these effects, complete fall risk assessments when initiating antipsychotic treatment and recurrently for patients on long-term antipsychotic therapy.

Usage in Pregnancy

Safety for the use of trifluoperazine hydrochloride during pregnancy has not been established. Therefore, it is not recommended that the drug be given to pregnant patients except when, in the judgment of the physician, it is essential. The potential benefits should clearly outweigh possible hazards. There are reported instances of prolonged jaundice, extrapyramidal signs, hyperreflexia or hyporeflexia in newborn infants whose mothers received phenothiazines.

Reproductive studies in rats given over 600 times the human dose showed an increased incidence of malformations above controls and reduced litter size and weight linked to maternal toxicity. These effects were not observed at half this dosage. No adverse effect on fetal development was observed in rabbits given 700 times the human dose nor in monkeys given 25 times the human dose.

Pregnancy

Nonteratogenic Effects

Neonates exposed to antipsychotic drugs, during the third trimester of pregnancy are at risk for extrapyramidal and/or withdrawal symptoms following delivery. There have been reports of agitation, hypertonia, hypotonia, tremor, somnolence, respiratory distress and feeding disorder in these neonates. These complications have varied in severity; while in some cases symptoms have been self-limited, in other cases neonates have required intensive care unit support and prolonged hospitalization.

Trifluoperazine hydrochloride should be used during pregnancy only if the potential benefit justifies the potential risk to the fetus.

Nursing Mothers

There is evidence that phenothiazines are excreted in the breast milk of nursing mothers. Because of the potential for serious adverse reactions in nursing infants from trifluoperazine, a decision should be made whether to discontinue nursing or to discontinue the drug, taking into account the importance of the drug to the mother.

PRECAUTIONS

General

Given the likelihood that some patients exposed chronically to antipsychotics will develop tardive dyskinesia, it is advised that all patients in whom chronic use is contemplated be given, if possible, full information about this risk. The decision to inform patients and/or their guardians must obviously take into account the clinical circumstances and the competency of the patient to understand the information provided.

Thrombocytopenia and anemia have been reported in patients receiving the drug. Agranulocytosis and pancytopenia have also been reported-warn patients to report the sudden appearance of sore throat or other signs of infection. If white blood cell and differential counts indicate cellular depression, stop treatment and start antibiotic and other suitable therapy.

Jaundice of the cholestatic type of hepatitis or liver damage has been reported. If fever with grippe-like symptoms occurs, appropriate liver studies should be conducted. If tests indicate an abnormality, stop treatment.

One result of therapy may be an increase in mental and physical activity. For example, a few patients with angina pectoris have complained of increased pain while taking the drug. Therefore, angina patients should be observed carefully and, if an unfavorable response is noted, the drug should be withdrawn.

Because hypotension has occurred, large doses and parenteral administration should be avoided in patients with impaired cardiovascular systems. To minimize the occurrence of hypotension after injection, keep patient lying down and observe for at least 1/2 hour. If hypotension occurs from parenteral or oral dosing, place patient in head-low position with legs raised. If a vasoconstrictor is required, norepinephrine bitartrate and phenylephrine hydrochloride are suitable. Other pressor agents, including epinephrine, should not be used as they may cause a paradoxical further lowering of blood pressure.

Since certain phenothiazines have been reported to produce retinopathy, the drug should be discontinued if ophthalmoscopic examination or visual field studies should demonstrate retinal changes.

An antiemetic action of trifluoperazine hydrochloride may mask the signs and symptoms of toxicity or overdosage of other drugs and may obscure the diagnosis and treatment of other conditions such as intestinal obstruction, brain tumor and Reye’s syndrome.

With prolonged administration at high dosages, the possibility of cumulative effects, with sudden onset of severe central nervous system or vasomotor symptoms, should be kept in mind.

Antipsychotic drugs elevate prolactin levels; the elevation persists during chronic administration. Tissue culture experiments indicate that approximately 1/3 of human breast cancers are prolactin-dependent in vitro, a factor of potential importance if the prescribing of these drugs is contemplated in a patient with a previously detected breast cancer. Although disturbances such as galactorrhea, amenorrhea, gynecomastia and impotence have been reported, the clinical significance of elevated serum prolactin levels is unknown for most patients. An increase in mammary neoplasms has been found in rodents after chronic administration of antipsychotic drugs. Published epidemiologic studies have shown inconsistent results when exploring the association between hyperprolactinemia and breast cancer.

Chromosomal aberrations in spermatocytes and abnormal sperm have been demonstrated in rodents treated with certain antipsychotics.

Because phenothiazines may interfere with thermoregulatory mechanisms, use with caution in persons who will be exposed to extreme heat.

As with all drugs which exert an anticholinergic effect, and/or cause mydriasis, trifluoperazine should be used with caution in patients with glaucoma.

Phenothiazines may diminish the effect of oral anticoagulants.

Phenothiazines can produce alpha-adrenergic blockade.

Concomitant administration of propranolol with phenothiazines results in increased plasma levels of both drugs.

Antihypertensive effects of guanethidine and related compounds may be counteracted when phenothiazines are used concurrently.

Thiazide diuretics may accentuate the orthostatic hypotension that may occur with phenothiazines.

Phenothiazines may lower the convulsive threshold; dosage adjustments of anticonvulsants may be necessary. Potentiation of anticonvulsant effects does not occur. However, it has been reported that phenothiazines may interfere with the metabolism of phenytoin and thus precipitate phenytoin toxicity.

Drugs which lower the seizure threshold, including phenothiazine derivatives, should not be used with metrizamide. As with other phenothiazine derivatives, trifluoperazine hydrochloride should be discontinued at least 48 hours before myelography, should not be resumed for at least 24 hours post procedure and should not be used for the control of nausea and vomiting occurring either prior to myelography or post procedure with metrizamide.

The presence of phenothiazines may produce false-positive phenylketonuria (PKU) test results.

Long-Term Therapy

To lessen the likelihood of adverse reactions related to cumulative drug effect, patients with a history of long-term therapy with trifluoperazine hydrochloride and/or other antipsychotics should be evaluated periodically to decide whether the maintenance dosage could be lowered or drug therapy discontinued.

Leukopenia, Neutropenia and Agranulocytosis

In clinical trial and post-marketing experience, events of leukopenia/neutropenia and agranulocytosis have been reported temporally related to antipsychotic agents.

Possible risk factors for leukopenia/neutropenia include preexisting low white blood cell count (WBC) and history of drug induced leukopenia/neutropenia. Patients with a preexisting low WBC or a history of drug induced leukopenia/neutropenia should have their complete blood count (CBC) monitored frequently during the first few months of therapy and should discontinue Trifluoperazine Hydrochloride Tablets, USP at the first sign of a decline in WBC in the absence of other causative factors.

Patients with neutropenia should be carefully monitored for fever or other symptoms or signs of infection and treated promptly if such symptoms occur. Patients with severe neutropenia (absolute neutrophil count < 1000/mm^3) should discontinue Trifluoperazine Hydrochloride Tablets, USP and have their WBC followed until recovery.

ADVERSE REACTIONS

Drowsiness, dizziness, skin reactions, rash, dry mouth, insomnia, amenorrhea, fatigue, muscular weakness, anorexia, lactation, blurred vision and neuromuscular (extrapyramidal) reactions.

Neuromuscular (Extrapyramidal) Reactions

These symptoms are seen in a significant number of hospitalized mental patients. They may be characterized by motor restlessness, be of the dystonic type, or they may resemble parkinsonism.

Depending on the severity of symptoms, dosage should be reduced or discontinued. If therapy is reinstituted, it should be at a lower dosage. Should these symptoms occur in children or pregnant patients, the drug should be stopped and not reinstituted. In most cases, barbiturates by suitable route of administration will suffice. (Or, injectable diphenhydramine hydrochloride may be useful.) In more severe cases, the administration of an antiparkinsonism agent, except levodopa, usually produces rapid reversal of symptoms. Suitable supportive measures such as maintaining a clear airway and adequate hydration should be employed.

Motor Restlessness

Symptoms may include agitation or jitteriness and sometimes insomnia. These symptoms often disappear spontaneously. At times these symptoms may be similar to the original neurotic or psychotic symptoms. Dosage should not be increased until these side effects have subsided.

If this phase becomes too troublesome, the symptoms can usually be controlled by a reduction of dosage or change of drug. Treatment with antiparkinsonism agents, benzodiazepines or propranolol may be helpful.

Dystonia

Class Effect

Symptoms of dystonia, prolonged abnormal contractions of muscle groups, may occur in susceptible individuals during the first few days of treatment. Dystonic symptoms include: spasm of the neck muscles, sometimes progressing to tightness of the throat, swallowing difficulty, difficulty breathing, and/or protrusion of the tongue. While these symptoms can occur at low doses, they occur more frequently and with greater severity with high potency and at higher doses of first generation antipsychotic drugs. An elevated risk of acute dystonia is observed in males and younger age groups.

Pseudoparkinsonism

Symptoms may include: mask-like facies; drooling; tremors; pill-rolling motion; cogwheel rigidity; and shuffling gait. Reassurance and sedation are important. In most cases these symptoms are readily controlled when an antiparkinsonism agent is administered concomitantly. Antiparkinsonism agents should be used only when required. Generally, therapy of a few weeks to 2 or 3 months will suffice. After this time, patients should be evaluated to determine their need for continued treatment. (Note: Levodopa has not been found effective in pseudoparkinsonism.) Occasionally it is necessary to lower the dosage of trifluoperazine hydrochloride or to discontinue the drug.

Tardive Dyskinesia

As with all antipsychotic agents, tardive dyskinesia may appear in some patients on long-term therapy or may appear after drug therapy has been discontinued. The syndrome can also develop, although much less frequently, after relatively brief treatment periods at low doses. This syndrome appears in all age groups. Although its prevalence appears to be highest among elderly patients, especially elderly women, it is impossible to rely upon prevalence estimates to predict at the inception of antipsychotic treatment which patients are likely to develop the syndrome. The symptoms are persistent and in some patients appear to be irreversible. The syndrome is characterized by rhythmical involuntary movements of the tongue, face, mouth or jaw (e.g., protrusion of tongue, puffing of cheeks, puckering of mouth, chewing movements). Sometimes these may be accompanied by involuntary movements of extremities. In rare instances, these involuntary movements of the extremities are the only manifestations of tardive dyskinesia. A variant of tardive dyskinesia, tardive dystonia, has also been described.

There is no known effective treatment for tardive dyskinesia; antiparkinsonism agents do not alleviate the symptoms of this syndrome. If clinically feasible, it is suggested that all antipsychotic agents be discontinued if these symptoms appear. Should it be necessary to reinstitute treatment, or increase the dosage of the agent, or switch to a different antipsychotic agent, the syndrome may be masked.

It has been reported that fine vermicular movements of the tongue may be an early sign of the syndrome and if the medication is stopped at that time the syndrome may not develop.

Adverse Reactions Reported with Trifluoperazine Hydrochloride or Other Phenothiazine Derivatives

Adverse effects with different phenothiazines vary in type, frequency, and mechanism of occurrence, i.e., some are dose related, while others involve individual patient sensitivity. Some adverse effects may be more likely to occur, or occur with greater intensity, in patients with special medical problems, e.g., patients with mitral insufficiency or pheochromocytoma have experienced severe hypotension following recommended doses of certain phenothiazines.

Neuroleptic Malignant Syndrome (NMS) has been reported in association with antipsychotic drugs. (See WARNINGS.)

Not all of the following adverse reactions have been observed with every phenothiazine derivative, but they have been reported with one or more and should be borne in mind when drugs of this class are administered: extrapyramidal symptoms (opisthotonos, oculogyric crisis, hyperreflexia, dystonia, akathisia, dyskinesia, parkinsonism) some of which have lasted months and even years–particularly in elderly patients with previous brain damage; grand mal and petit mal convulsions, particularly in patients with EEG abnormalities or history of such disorders; altered cerebrospinal fluid proteins; cerebral edema; intensification and prolongation of the action of central nervous system depressants (opiates, analgesics, antihistamines, barbiturates, alcohol), atropine, heat, organophosphorus insecticides; autonomic reactions (dryness of mouth, nasal congestion, headache, nausea, constipation, obstipation, adynamic ileus, ejaculatory disorders/impotence, priapism, atonic colon, urinary retention, miosis and mydriasis); reactivation of psychotic processes, catatonic-like states; hypotension (sometimes fatal); cardiac arrest; blood dyscrasias (pancytopenia, thrombocytopenic purpura, leukopenia, agranulocytosis, eosinophilia, hemolytic anemia, aplastic anemia); liver damage (jaundice, biliary stasis); endocrine disturbances (hyperglycemia, hypoglycemia, glycosuria, lactation, galactorrhea, gynecomastia, menstrual irregularities, false-positive pregnancy tests); skin disorders (photosensitivity, itching, erythema, urticaria, eczema up to exfoliative dermatitis); other allergic reactions (asthma, laryngeal edema, angioneurotic edema, anaphylactoid reactions); peripheral edema; reversed epinephrine effect; hyperpyrexia; increased appetite; increased weight; a systemic lupus erythematosus-like syndrome; pigmentary retinopathy; with prolonged administration of substantial doses, skin pigmentation, epithelial keratopathy, and lenticular and corneal deposits.

EKG changes-particularly nonspecific, usually reversible Q and T wave distortions-have been observed in some patients receiving phenothiazine antipsychotics. Although phenothiazines cause neither psychic nor physical dependence, sudden discontinuance in long-term psychiatric patients may cause temporary symptoms, e.g., nausea and vomiting, dizziness, tremulousness.

Note:There have been occasional reports of sudden death in patients receiving phenothiazines. In some cases, the cause appeared to be cardiac arrest or asphyxia due to failure of the cough reflex.

OVERDOSAGE

(See also under ADVERSE REACTIONS.)

Symptoms

Primarily involvement of the extrapyramidal mechanism producing some of the dystonic reactions described above. Symptoms of central nervous system depression to the point of somnolence or coma. Agitation and restlessness may also occur. Other possible manifestations include convulsions, EKG changes and cardiac arrhythmias, fever and autonomic reactions such as hypotension, dry mouth and ileus.

Treatment

It is important to determine other medications taken by the patient since multiple dose therapy is common in overdosage situations. Treatment is essentially symptomatic and supportive. Early gastric lavage is helpful. Keep patient under observation and maintain an open airway, since involvement of the extrapyramidal mechanism may produce dysphagia and respiratory difficulty in severe overdosage. Do not attempt to induce emesis because a dystonic reaction of the head or neck may develop that could result in aspiration of vomitus.Extrapyramidal symptoms may be treated with antiparkinsonism drugs, barbiturates, or diphenhydramine hydrochloride. See prescribing information for these products. Care should be taken to avoid increasing respiratory depression. If administration of a stimulant is desirable, amphetamine, dextroamphetamine, or caffeine with sodium benzoate is recommended. Stimulants that may cause convulsions (e.g., picrotoxin or pentylenetetrazol) should be avoided.

If hypotension occurs, the standard measures for managing circulatory shock should be initiated. If it is desirable to administer a vasoconstrictor, norepinephrine bitartrate and phenylephrine hydrochloride are most suitable. Other pressor agents, including epinephrine, are not recommended because phenothiazine derivatives may reverse the usual elevating action of these agents and cause a further lowering of blood pressure.

Limited experience indicates that phenothiazines are notdialyzable.

DOSAGE AND ADMINISTRATION-ADULTS

Dosage should be adjusted to the needs of the individual. The lowest effective dosage should always be used. Dosage should be increased more gradually in debilitated or emaciated patients. When maximum response is achieved, dosage may be reduced gradually to a maintenance level. Because of the inherent long action of the drug, patients may be controlled on convenient b.i.d. administration; some patients may be maintained on once a day administration.

When trifluoperazine hydrochloride is administered by intramuscular injection, equivalent oral dosage may be substituted once symptoms have been controlled.

Note: Although there is little likelihood of contact dermatitis due to the drug, persons with known sensitivity to phenothiazine drugs should avoid direct contact.

Elderly Patients

In general, dosages in the lower range are sufficient for most elderly patients. Since they appear to be more susceptible to hypotension and neuromuscular reactions, such patients should be observed closely. Dosage should be tailored to the individual, response carefully monitored, and dosage adjusted accordingly. Dosage should be increased more gradually in elderly patients.

Non-Psychotic Anxiety

Usual dosage is 1 mg or 2 mg twice daily. Do not administer at doses of more than 6 mg per day or for longer than 12 weeks.

Schizophrenia

Oral

Usual starting dosage is 2 mg to 5 mg b.i.d. (Small or emaciated patients should always be started on the lower dosage.)

Most patients will show optimum response on 15 mg or 20 mg daily, although a few may require 40 mg a day or more. Optimum therapeutic dosage levels should be reached within 2 or 3 weeks.

DOSAGE AND ADMINISTRATION-SCHIZOPHRENIA IN CHILDREN

Dosage should be adjusted to the weight of the child and severity of the symptoms. These dosages are for children, ages 6 to 12, who are hospitalized or under close supervision.

Oral

The starting dosage is 1 mg administered once a day or b.i.d. Dosage may be increased gradually until symptoms are controlled or until side effects become troublesome.

While it is usually not necessary to exceed dosages of 15 mg daily, some older children with severe symptoms may require higher dosages.

HOW SUPPLIED

Trifluoperazine Hydrochloride Tablets, USP are available containing trifluoperazine hydrochloride, USP equivalent to 2 mg of trifluoperazine.

The 2 mg tablets are white, film-coated, round, unscored tablets debossed with T4 on one side of the tablet and M on the other side. They are available as follows:

NDC: 70518-2095-00

PACKAGING: 30 in 1 BLISTER PACK

Store at 20° to 25°C (68° to 77°F). [See USP Controlled Room Temperature.]

Dispense in a tight, light-resistant container as defined in the USP using a child-resistant closure.

Repackaged and Distributed By:

Remedy Repack, Inc.

625 Kolter Dr. Suite #4 Indiana, PA 1-724-465-8762

PACKAGE LABEL

DRUG: Trifluoperazine Hydrochloride

GENERIC: trifluoperazine hydrochloride

DOSAGE: TABLET, FILM COATED

ADMINSTRATION: ORAL

NDC: 70518-2095-0

COLOR: white

SHAPE: ROUND

SCORE: No score

SIZE: 8 mm

IMPRINT: M;T4

PACKAGING: 30 in 1 BLISTER PACK

ACTIVE INGREDIENT(S):

- TRIFLUOPERAZINE HYDROCHLORIDE 2mg in 1

INACTIVE INGREDIENT(S):

- SILICON DIOXIDE
- CROSCARMELLOSE SODIUM
- HYPROMELLOSE, UNSPECIFIED
- LACTOSE MONOHYDRATE
- MAGNESIUM STEARATE
- MICROCRYSTALLINE CELLULOSE
- POLYDEXTROSE
- POLYETHYLENE GLYCOL, UNSPECIFIED
- STARCH, CORN
- SODIUM LAURYL SULFATE
- TITANIUM DIOXIDE
- TRIACETIN